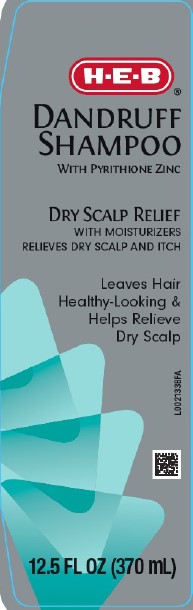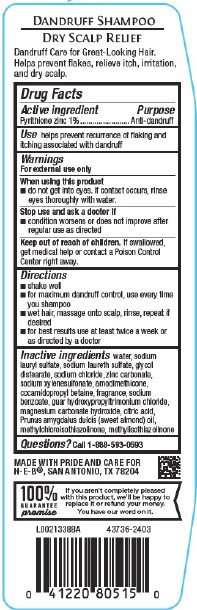 DRUG LABEL: Dry Scalp Dandruff
NDC: 37808-281 | Form: SHAMPOO
Manufacturer: H E B
Category: otc | Type: HUMAN OTC DRUG LABEL
Date: 20260224

ACTIVE INGREDIENTS: PYRITHIONE ZINC 10 mg/1 mL
INACTIVE INGREDIENTS: WATER; SODIUM LAURYL SULFATE; SODIUM LAURETH SULFATE; GLYCOL DISTEARATE; SODIUM CHLORIDE; ZINC CARBONATE; SODIUM XYLENESULFONATE; AMODIMETHICONE (800 CST); COCAMIDOPROPYL BETAINE; SODIUM BENZOATE; GUAR HYDROXYPROPYLTRIMONIUM CHLORIDE (1.7 SUBSTITUENTS PER SACCHARIDE); MAGNESIUM CARBONATE HYDROXIDE; CITRIC ACID MONOHYDRATE; ALMOND OIL; METHYLCHLOROISOTHIAZOLINONE; METHYLISOTHIAZOLINONE

HEB 281.007/281AK-AN
Dandruff Shampoo, Dry Scalp

Claims

DANDRUFF SHAMPOO

DRY SCALP RELIEF

Dandruff Care for Great Looking Hair. Helps prevent flakes, relieve itch, irritation, and dry scalp.

Active ingredient

Pyrithione zinc 1%

Purpose

Anti-dandruff

Use

helps prevent recurrence of flaking and itching associated with dandruff

Warnings

For external use only

When using this product

- do not get into eyes. If contact occurs, rinse eyes thoroughly with water.

Stop use and ask a doctor if

- condition worsens or does not improve after regular use as directed

Keep out of reach of children.

If swallowed, get medical help or contact a Poison Control Center right away.

Directions

- shake well
- for maximum dandruff control, use everytime you shampoo
- wet hair, massage onto scalp, rinse, repeat if desired
- for best results use at least twice a week or as directed by a doctor

Inactive ingredients

water, sodium lauryl sulfate, sodium laureth sulfate, glycol distearate, sodium chloride, zinc carbonate, sodium xylenesulfonate, amodimethicoe, cocamidopropyl betaine, fragrance, sodium benzoate, guar hydroxypropyltrimonium chloride, magnesium carbonate hydroxide, citric acid, Prunus amygdalus dulcis (sweet almond) oil, methylchloroisothiazolinone, methylisothiazolinone

Questions?

Call 1-888-593-0593

Adverse reaction

MADE WITH PRIDE AND CARE FOR H-E-B®, SAN ANTONIO, TX 78204

100% GUARANTEE promise

If you aren't completely pleased with this product, we'll be happy to replace it or refund your money.

You have our word on it.

Principal display panel

H-E-B®

DANDRUFF SHAMPOO

WITH PYRITHIONE ZINC

DRY SCALP RELIEF

WITH MOISTURIZERS

RELIEVES DRY SCALP AND ITCH

Leaves Hair Healthy-Looking & Helps Relieve Dry Scalp

12.5 FL OZ (370 mL)